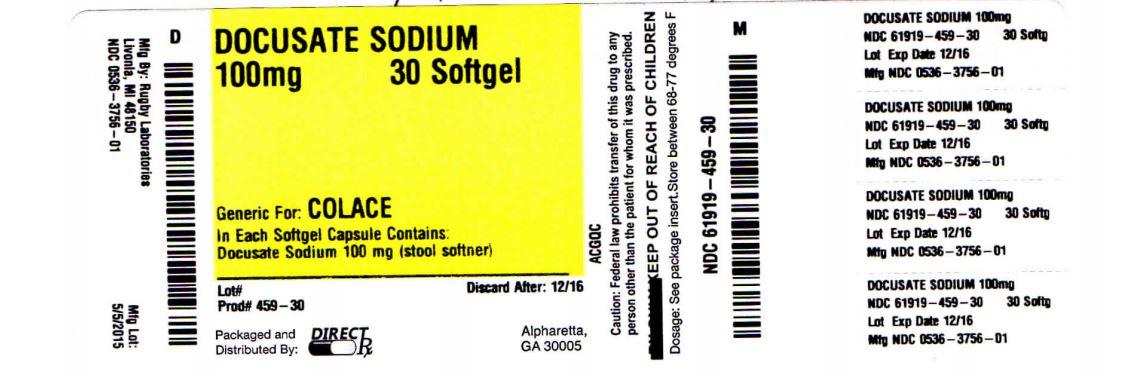 DRUG LABEL: DOCUSATE SODIUM
NDC: 61919-459 | Form: CAPSULE, LIQUID FILLED
Manufacturer: DIRECT RX
Category: otc | Type: HUMAN OTC DRUG LABEL
Date: 20150514

ACTIVE INGREDIENTS: DOCUSATE SODIUM 100 mg/1 1
INACTIVE INGREDIENTS: FD&C RED NO. 40; FD&C YELLOW NO. 6; GELATIN; GLYCERIN; POLYETHYLENE GLYCOLS; PROPYLENE GLYCOL; WATER; SORBITOL

DOCUSATE SODIUM

OTC - ACTIVE INGREDIENT SECTION

Docusate Sodium 100 mg

OTC - PURPOSE SECTION

Stool softener

INDICATIONS & USAGE SECTION

- for prevention of dry, hard stools
- for relief of occasional constipation

This product generally produces a bowel movement within 12 to 72 hours.

WARNINGS SECTION

Do not use

- if you are currently taking mineral oil, unless directed by a doctor
- when abdominal pain, nausea, or vomiting are present
- for longer than 1 week, unless directed by a doctor

Ask a doctor before use if

if you notice a sudden change in bowel habits that persists over a period of 2 weeks.

Stop use and ask a doctor if

- you have rectal bleeding
- you fail to have a bowel movement after use

These could be signs of a serious condition.

If pregnant or breast-feeding,

ask a health care professional before use.

Keep out of reach of children.

In case of overdose, get medical help or contact a Poison Control Center right away.

DOSAGE & ADMINISTRATION SECTION

Directions

adults and children over 12 years of age | take 1 to 3 softgels preferably at bedtime
children 6-12 years of age | take 1 softgel at bedtime
children under 6 years | ask a doctor

Other information

- each softgel contains: sodium 6 mg
- store between 15º-30ºC (59º-86ºF)

Questions or comments?

1-800-645-2158

Principal Display Panel

COMPARE TO ACTIVE INGREDIENT IN COLACE®*

NON-HABIT FORMING

Stool Softener Laxative

Docusate Sodium USP, 100 mg

SOFTGEL CAPSULES

TAMPER EVIDENT: DO NOT USE IF IMPRINTED SAFETY SEAL UNDER CAP IS BROKEN OR MISSING

*Rugby Laboratories is not affiliated with the owner of the trademark Colace®.

Distributed by: Rugby Laboratories

31778 Enterprise Drive

Livonia, MI 48150

OTC - KEEP OUT OF REACH OF CHILDREN SECTION

In case of overdose, get medical help or contact a Poison Control Center right away.

INACTIVE INGREDIENT SECTION

edible white ink, FD&C red #40, FD&C yellow #6, gelatin, glycerin, polyethylene glycol, propylene glycol, purified water, sorbitol special.